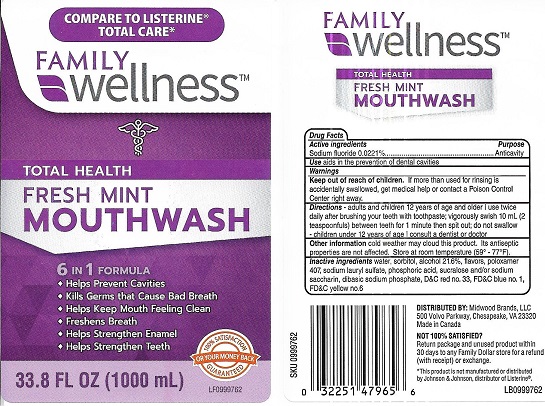 DRUG LABEL: Family Wellness
NDC: 55319-233 | Form: MOUTHWASH
Manufacturer: Family Dollar Services Inc.
Category: otc | Type: HUMAN OTC DRUG LABEL
Date: 20210823

ACTIVE INGREDIENTS: SODIUM FLUORIDE 0.02 g/100 mL
INACTIVE INGREDIENTS: D&C RED NO. 33; SORBITOL; PHOSPHORIC ACID; SUCRALOSE; POLOXAMER 407; SODIUM PHOSPHATE, DIBASIC; WATER; ALCOHOL; FD&C YELLOW NO. 6; SODIUM LAURYL SULFATE; SACCHARIN SODIUM; FD&C BLUE NO. 1

Family Wellness Fresh Mint Anticavity Mouthwash

Drug Facts

Active ingredient
Sodium fluoride 0.0221%

Purpose

Anticavity

INDICATIONS AND USAGE

Useaids in the prevention of dental cavities

Warnings

Keep out of reach of children. If more than used for rinsing is accidentally swallowed, get medical help or contact a Poison Control Center right away.

Directions

- adults and children 12 years of age and older: use twice daily after brushing your teeth with toothpaste; vigorously swish 10 mL (2 teaspoonfuls) between teeth for 1 minute then spit out; do not swallow
- children under 12 years of age: consult a dentist or doctor

Other information cold weather may cloud this product. Its antiseptic properties are not affected . Store at room temperature (59° - 77°F)

INACTIVE INGREDIENT

Inactive ingredients water, sorbitol, alcohol 21.6%, flavors, poloxamer 407, sodium lauryl sulfate, phosphoric acid, sucralose and/or sodium saccharin, dibasic sodium phosphate, D&C red no. 33, FD&C blue no. 1, FD&C yellow no. 6.

DISTRIBUTED BY: Midwood Brands, LLC

500 Volvo Parkway, Chesapeake, VA 23320

Made in Canada

* This product is not manufactured or distributed by Johnson & Johnson, distributor of Listerine®.

PACKAGE LABEL

COMPARE TO LISTERINE® TOTAL CARE*

FAMILY wellness™

TOTAL HEALTH

FRESH MINT

MOUTHWASH

6 IN 1 FORMULA

- Helps Prevent Cavities
- Kills Germs that Cause Bad Breath
- Helps Keep Mouth Feeling Clean
- Freshens Breath
- Helps Strengthen Enamel
- Helps Strengthen Teeth

33.8 FL OZ (1000 mL)